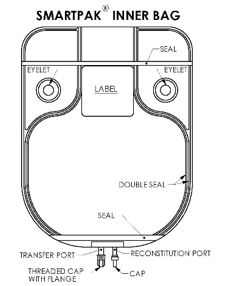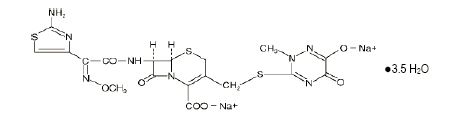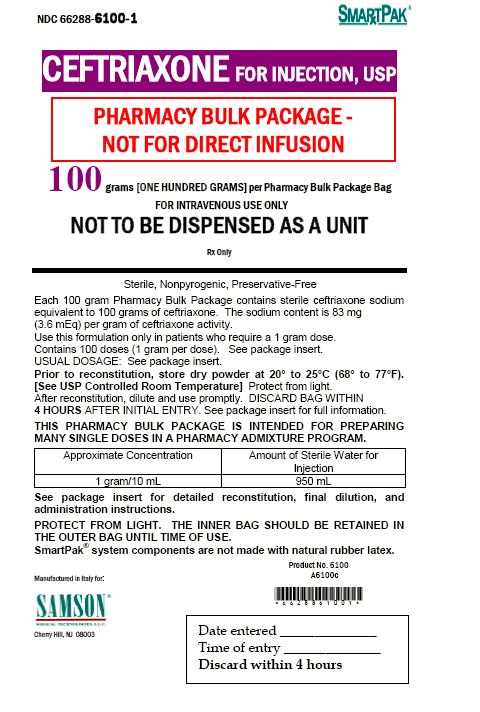 DRUG LABEL: Ceftriaxone
NDC: 66288-6100 | Form: INJECTION, POWDER, FOR SOLUTION
Manufacturer: Samson Medical Technologies, LLC
Category: prescription | Type: HUMAN PRESCRIPTION DRUG LABEL
Date: 20230115

ACTIVE INGREDIENTS: CEFTRIAXONE SODIUM 100 g/1 1

HIGHLIGHTS OF PRESCRIBING INFORMATION

These highlights do not include all the information needed to use CEFTRIAXONE FOR INJECTION safely and effectively. See full prescribing information for CEFTRIAXONE FOR INJECTION.
CEFTRIAXONE FOR INJECTION, USP
Ceftriaxone for Injection, for intravenous use
Initial U.S. Approval: 1984

1 INDICATIONS AND USAGE

Ceftriaxone for Injection, USP is a cephalosporin antibacterial indicated for the treatment of the following infections caused by susceptible isolates of the designated bacteria: Lower Respiratory Tract Infections (1.1); Skin and Skin Structure Infections (1.2); Complicated and Uncomplicated Urinary Tract Infections (1.3); Pelvic Inflammatory Disease (1.4); Bacterial Septicemia (1.5); Bone and Joint infections (1.6); Intra-abdominal Infections (1.7); Meningitis (1.8); and Surgical Prophylaxis (1.9).

2 DOSAGE AND ADMINISTRATION

For intravenous use only over approximately 30 minutes. (2)

THIS IS A PHARMACY BULK PACKAGE – NOT FOR DIRECT INJECTION.

Ceftriaxone for Injection USP, Pharmacy Bulk Package bag SmartPak® should be used only in patients who require a 1 gram dose and not any fraction thereof. Ceftriaxone for Injection USP, Pharmacy Bulk Package bag SmartPak® should not be used in patients who require less than the 1 gram dose of ceftriaxone (2.1).

Recommended Dosing Schedule for Ceftriaxone for Injection, USP
Site and Type of Infection | Dose | Frequency | Total Daily Dose
Usual Adult Dose | 1 to 2 grams | Once a day or in equally divided doses every 12 hours | Should not exceed 4 grams [Patients with hepatic impairment and significant renal impairment should not receive more than 2 grams per day of ceftriaxone.]
Surgical prophylaxis | 1 gram I.V. once | ½ to 2 hours before surgery
Meningitis | 100 mg per kg | Once a day or in equally divided doses every 12 hours | Should not exceed 4 grams
Skin and Skin Structure Infections | 50 mg per kg to 75 mg per kg | Once a day or in equally divided doses every 12 hours | Should not exceed 2 grams
Serious Infections other than Meningitis | 50 mg per kg to 75 mg per kg | Every 12 hours | Should not exceed 2 grams

Ceftriaxone for Injection USP, Pharmacy Bulk Package bag SmartPak® should be used only in patients who require a 1 gram dose and not any fraction thereof. Ceftriaxone for Injection USP, Pharmacy Bulk Package bag SmartPak® should not be used in patients who require less than the 1 gram dose of ceftriaxone. (2.1)

3 DOSAGE FORMS AND STRENGTHS

- Pharmacy Bulk Package bags, 100 grams (3)
  THIS IS A PHARMACY BULK PACKAGE – NOT FOR DIRECT INJECTION

4 CONTRAINDICATIONS

- Anaphylaxis to ceftriaxone or other cephalosporin class antibacterials, penicillins or other beta-lactam antibacterials (4.1)

5 WARNINGS AND PRECAUTIONS

- Hypersensitivity reactions: Include anaphylaxis and serious skin reactions. Cross hypersensitivity may occur in up to 10% of patients with a history of penicillin allergy. If an allergic reaction occurs, discontinue the drug (5.1).
- Interaction with Calcium-containing products: Precipitation can occur. Do not administer simultaneously with calcium-containing I.V. solutions (5.2).
- Neurological adverse reactions: Serioous neurological adverse reactions have been reported during postmarketing surveillance. If serious adverse reactions occur, discontinue the drug and institute appropriate supportive measures. (5.3)
- Clostridium difficile-associated diarrhea: May range from mild diarrhea to fatal colitis. Evaluate if diarrhea occurs (5.4).
- Hemolytic Anemia: Severe cases of hemolytic anemia, including fatalities in adults and children, have been reported. If anemia is diagnosed, discontinue the drug until the etiology is determined. (5.5)

6 ADVERSE REACTIONS

The most common adverse reactions occurring in >2% of patients receiving ceftriaxone include diarrhea, eosinophilia, thrombocytosis, leukopenia, and elevations of SGOT and SGPT. (6)

To report SUSPECTED ADVERSE REACTIONS, contact Samson Medical Technologies, L.L.C. at 1-877-418-3600 or FDA at 1-800-FDA-1088 or www.fda.gov/medwatch.

7 DRUG INTERACTIONS

- Vancomycin, amsacrine, aminoglycosides and fluconazole are physically incompatible. (7.1)
- Calcium-containing products: precipitation can occur. (7.2)

8 USE IN SPECIFIC POPULATIONS

- Hepatic impairment: Patients with both hepatic and renal impairment should not receive more than 2 grams of ceftriaxone per day. (5.7)
- Renal Impairment: This formulation of Ceftriaxone for Injection USP – Pharmacy Bulk Package bag, SmartPak® should not be used in renally impaired patients who require less than the 1 gram dose of ceftriaxone. Patients with both hepatic and renal impairment should not receive more than 2 grams of ceftriaxone per day. (5.7)
- Pediatric Patients: This formulation of Ceftriaxone for Injection USP – Pharmacy Bulk Package bag, SmartPak® should not be used in pediatric patients who require less than the 1 gram adult dose of ceftriaxone. (2.2, 8.4)

12.4 Microbiology

PHARMACY BULK PACKAGE -
NOT FOR DIRECT INFUSION

To reduce the development of drug-resistant bacteria and maintain the effectiveness of ceftriaxone and other antibacterial drugs, ceftriaxone should be used only to treat or prevent infections that are proven or strongly suspected to be caused by bacteria. (12.4)

FULL PRESCRIBING INFORMATION

1 INDICATIONS AND USAGE

To reduce the development of drug-resistant bacteria and maintain the effectiveness of Ceftriaxone for Injection and other antibacterial drugs, Ceftriaxone for Injection should be used only to treat or prevent infections that are proven or strongly suspected to be caused by susceptible bacteria. When culture and susceptibility information are available, they should be considered in selecting or modifying antibacterial therapy. In the absence of such data, local epidemiology and susceptibility patterns may contribute to the empiric selection of therapy.

Ceftriaxone for Injection is indicated for the treatment of the following infections when caused by susceptible bacteria:

1.1 Lower Respiratory Tract Infections

Lower respiratory tract infections caused by Streptococcus pneumoniae, Staphylococcus aureus, Haemophilus influenzae, Haemophilus parainfluenzae, Klebsiella pneumoniae, Escherichia coli, Enterobacter aerogenes, Proteus mirabilis or Serratia marcescens.

1.2 Skin and Skin Structure Infections

Skin and skin structure infections caused by Staphylococcus aureus, Staphylococcus epidermidis, Streptococcus pyogenes, Viridans group streptococci, Escherichia coli, Enterobacter cloacae, Klebsiella oxytoca, Klebsiella pneumoniae, Proteus mirabilis, Morganella morganii [The efficacy for these organisms in this organ system were studied in fewer than ten infections.] , Pseudomonas aeruginosa, Serratia marcescens, Acinetobacter calcoaceticus, Bacteroides fragilis or Peptostreptococcus species.

1.3 Complicated and Uncomplicated Urinary Tract Infections

Complicated and uncomplicated urinary tract infections caused by Escherichia coli, Proteus mirabilis, Proteus vulgaris, Morganella morganii or Klebsiella pneumoniae.

1.4 Pelvic Inflammatory Disease

Pelvic inflammatory disease caused by Neisseria gonorrhoeae. Ceftriaxone sodium, like other cephalosporins, has no activity against Chlamydia trachomatis. Therefore, when cephalosporins are used in the treatment of patients with pelvic inflammatory disease and Chlamydia trachomatis is one of the suspected pathogens, appropriate antichlamydial coverage should be added.

1.5 Bacterial Septicemia

Bacterial septicemia caused by Staphylococcus aureus, Streptococcus pneumoniae, Escherichia coli, Haemophilus influenzae or Klebsiella pneumoniae.

1.6 Bone and Joint Infections

Bone and joint infections caused by Staphylococcus aureus, Streptococcus pneumoniae, Escherichia coli, Proteus mirabilis, Klebsiella pneumoniae or Enterobacter species.

1.7 Intra-abdominal Infections

Intra-abdominal infections caused by Escherichia coli, Klebsiella pneumoniae, Bacteroides fragilis, Clostridium species or Peptostreptococcus species.

1.8 Meningitis

Meningitis caused by Haemophilus influenzae, Neisseria meningitidis or Streptococcus pneumoniae. Ceftriaxone sodium has also been used successfully in a limited number of cases of meningitis and shunt infection caused by Staphylococcus epidermidis and Escherichia coli; however, the efficacy for these organisms in this organ system were studied in fewer than ten infections.

1.9 Surgical Prophylaxis

The preoperative administration of a single 1 gram dose of ceftriaxone may reduce the incidence of postoperative infections in patients undergoing surgical procedures classified as contaminated or potentially contaminated (e.g., vaginal or abdominal hysterectomy or cholecystectomy for chronic calculous cholecystitis in high-risk patients, such as those over 70 years of age, with acute cholecystitis not requiring therapeutic antimicrobials, obstructive jaundice or common duct bile stones) and in surgical patients for whom infection at the operative site would present serious risk (e.g., during coronary artery bypass surgery). Although ceftriaxone sodium has been shown to have been as effective as cefazolin in the prevention of infection following coronary artery bypass surgery, no placebo-controlled trials have been conducted to evaluate any cephalosporin antibacterial in the prevention of infection following coronary artery bypass surgery.

2 DOSAGE AND ADMINISTRATION

Ceftriaxone for Injection USP, Pharmacy Bulk Package bag SmartPak® should be used only in patients who require a 1 gram dose and not any fraction thereof.

Ceftriaxone for Injection USP, Pharmacy Bulk Package bag SmartPak® should not be used in patients who require less than the 1 gram dose of Ceftriaxone.

THIS PHARMACY BULK PACKAGE REQUIRES RECONSTITUTION WITH STERILE WATER FOR INJECTION, USP TO A CONCENTRATION OF 100 mg per mL AND FURTHER DILUTION IN 50 mL OF A COMPATIBLE SOLUTION.

THIS IS A PHARMACY BULK PACKAGE – NOT FOR DIRECT INJECTION

USE THIS FORMULATION OF CEFTRIAXONE ONLY IN PATIENTS WHO REQUIRE A 1 GRAM DOSE.

2.1 Adult Population

Ceftriaxone for Injection, USP, Pharmacy Bulk Package bag SmartPak® should be used only in patients who require a 1 gram dose and not any fraction thereof.

Ceftriaxone for Injection USP Pharmacy Bulk Package bag SmartPak® should not be used in patients who require less than the 1 gram dose of Ceftriaxone.

Ceftriaxone for Injection should be reconstituted with Sterile Water for Injection, USP to a concentration of 100 mg per mL and further diluted in 50 mL of a compatible solution.

The recommended adult dosages are outlined in Table 1. Ceftriaxone for Injection, USP, Pharmacy Bulk Package SmartPak® should be used only in patients who require a 1 gram dose and not any fraction thereof.

Ceftriaxone should be administered intravenously (I.V.) over approximately 30 minutes.

The usual duration of therapy is 4 to 14 days; in complicated infections, longer therapy may be required. When treating infections caused by Streptococcus pyogenes, therapy should be continued for at least 10 days.

Table 1: Recommended Dosing Schedule for Ceftriaxone for Injection, USP
Site and Type of Infection | Dose | Frequency | Total Daily Dose
Usual Adult Dose | 1 gram to 2 grams | Once a day or in equally divided doses every 12 hours | Should not exceed 4 grams*
Surgical prophylaxis | 1 gram I.V. once | ½ to 2 hours before surgery
Skin and Skin Structure Infections | 50 to 75 mg per kg | Once a day or in equally divided doses every 12 hours | Should not exceed 2 grams
Meningitis | 100 mg per kg | Once a day or in equally divided doses every 12 hours | Should not exceed 4 grams*
Serious Infections other than Meningitis | 50 to 75 mg per kg | Every 12 hours | Should not exceed 2 grams
*Patients with hepatic impairment and significant renal impairment should not receive more than 2 grams per day of ceftriaxone.
**This formulation of Ceftriaxone for Injection USP, Pharmacy Bulk Package bag SmartPak® should not be used in patients who require less than the 1 gram dose of ceftriaxone.

2.2 Pediatric Patients

To prevent unintentional overdose, this product should not be used in pediatric patients who require less than the adult 1 gram dose of ceftriaxone. [see Use in Specific Populations (8.4)]

2.3 Preparation for Use of Ceftriaxone for Injection, USP, Pharmacy Bulk Package bags, SmartPak®

Ceftriaxone for Injection, USP Pharmacy Bulk Package bag SmartPak® should be used only in patients who require a 1 gram dose and not any fraction thereof.

Ceftriaxone for Injection USP, Pharmacy Bulk Package SmartPak® bag should not be used in patients who require less than the 1 gram dose of ceftriaxone.

Directions for Proper Use of a Pharmacy Bulk Package

- NOT FOR DIRECT INFUSION. The Pharmacy Bulk Package is for use in the hospital pharmacy admixture service only in a suitable work area, such as a laminar flow hood. Using aseptic technique, the container closure may be penetrated only one time after reconstitution using a suitable sterile dispensing set or transfer device that allows measured dispensing of the contents. Use of a syringe and needle is not recommended as it may cause leakage. The withdrawal of container contents should be accomplished without delay. However, should this not be possible, a maximum time of 4 HOURS from initial reconstitution port closure entry is permitted to complete fluid transfer operations. This time limit should begin with the introduction of the solvent or diluent into the Pharmacy Bulk Package. Discard any unused portion after 4 HOURS. This pharmacy bulk package is not intended to be dispensed as a unit
- PRIOR TO RECONSTITUTION: DO NOT USE THE INNER BAG IF PARTICULATE OR FOREIGN MATTER IS PRESENT, IF THE DRY POWDER IS DARK YELLOW OR BROWN, IF THE SEALS ARE NOT INTACT, OR IF THERE IS ANY OTHER DAMAGE TO THE BAG. IN SUCH CASES, DISCARD THE BAG IMMEDIATELY.
- After initial reconstitution port entry, use entire contents of the Pharmacy Bulk Package promptly. Any unused portion must be discarded after 4 HOURS.
- Gather the following items prior to the reconstitution of the product: Appropriate number of bags of Sterile Water for Injection and, depending upon the method of filling, appropriate sterile tubing and adapters.
- Parenteral drug products should be inspected visually for particulate matter and discoloration prior to administration. Use only if solution is clear.
- Do not use diluents containing calcium, such as Ringer’s solution or Hartmann’s solution, to reconstitute Ceftriaxone for Injection SmartPak® Pharmacy Bulk Package or to further dilute a reconstituted solution for intravenous administration. Particulate formation can result.

INSTRUCTION FOR RECONSTITUTION OF THE PHARMACY BULK PACKAGE BAG SmartPak®

The entire contents of the bag and the preparation process (reconstitution and dilution) should be completed within 4 hours of initial entry.

- Document the date and time reconstitution starts in the designated place on the container label. The entire contents of the bag must be used within 4 hours from the time of initial entry.
- Remove the translucent unthreaded cap from the reconstitution (smaller) port and discard it.
- Reconstitute the powder through the reconstitution (smaller) port, using Sterile Water for Injection according to the Table 2 below:

Table 2: Reconstitution Table
SmartPak® Bag Size | Amount of Sterile Water [Do not use diluents containing calcium, such as Ringer’s solution or Hartmann’s solution, to reconstitute or further dilute reconstituted ceftriaxone because a precipitate can form. STERILE WATER FOR INJECTION IS THE ONLY RECOMMENDED DILUENT FOR RECONSTITUTION. [see Warnings and Precautions [(5.2)].] | Approximate Concentration
100 grams | 950 mL | 100 mg/mL (1 g/10 mL)

- After reconstitution is complete, remove the transfer needle from the reconstitution port.
- Place the bag on a flat surface of a laminar flow hood and mix for at least 15 minutes by rocking gently from side to side. CAUTION: To avoid possible leakage caused by the heavy weight of the added water, do not shake vigorously or pull strongly on the bag.
- When foam dissipates, visually inspect the bag to verify the solution is clear, colorless to pale yellow and free of particulate matter. DO NOT USE THE INNER BAG IF PARTICULATE OR FOREIGN MATTER IS PRESENT.
- Unscrew the clear threaded cap from the transfer (larger) port and discard it. Attach sterile tubing and filling adapter unit to the transfer port.
- Reconstituted solution can now be transferred using the transfer port and the filling adapter.

It should be noted that the spike placed into the transfer port of the Pharmacy Bulk Package SmartPak® is NEVER removed during this procedure and that the reconstitution port is self-sealing.

Dilution

- Hang the bag from two eyelets.
- Following reconstitution, transfer 10 mL of the reconstituted solution into transfusion bags, each containing 50 mL of one of the compatible solutions below.
  Compatible solutions for dilution are the following:
  Sodium Chloride Injection, USP
  5% Dextrose Injection, USP
- Dilution should be completed within the 4 hour preparation process.
- When diluted according to the instructions above, ceftriaxone is stable for 48 hours at room temperature or for 10 days if stored under refrigeration (5°C or 41°F).

Important Administration Instructions

- Do not use diluents containing calcium, such as Ringer’s solution or Hartmann’s solution, to reconstitute Ceftriaxone for Injection SmartPak® Pharmacy Bulk Package or to further dilute a reconstituted solution for intravenous administration. Particulate formation can result. Precipitation of ceftriaxone-calcium can also occur when ceftriaxone is mixed with calcium-containing solutions in the same intravenous administration line. Ceftriaxone for Injection, USP must not be administered simultaneously with calcium-containing intravenous solutions, including continuous calcium-containing infusions, such as parenteral nutrition via a Y-site. However, in patients other than neonates, Ceftriaxone for Injection, USP and calcium-containing solutions may be administered sequentially of one another if the infusion lines are thoroughly flushed between infusions with a compatible fluid [see Warnings and Precautions (5.2)].
- Prior to administration, parenteral products should be inspected visually for particulate matter and discoloration whenever solution and container permit.
- Administer diluted ceftriaxone solutions intravenously over approximately 30 minutes.
- After the indicated stability times, unused portions of solutions should be discarded.
- Vancomycin, amsacrine, aminoglycosides and fluconazole are physically incompatible with ceftriaxone in admixtures. When any of these drugs are to be administered concomitantly with ceftriaxone by intermittent intravenous infusion, it is recommended that they be given sequentially with thorough flushing of the intravenous lines with 0.9% Sodium Chloride Injection or 5% Dextrose in Water (D5W) between the administrations.
- Ceftriaxone for Injection should not be physically mixed with or piggybacked into solutions containing other antimicrobial drugs due to possible incompatibility [see Drug Interactions (7.1)].
- There have been no reports of an interaction between ceftriaxone and oral calcium-containing products or interaction between intramuscular ceftriaxone and calcium-containing products (intravenous or oral).

3 DOSAGE FORMS AND STRENGTHS

- 100 grams Ceftriaxone for Injection, USP, Pharmacy Bulk Package bag, SmartPak® THIS IS A PHARMACY BULK PACKAGE – NOT FOR DIRECT INJECTION

4 CONTRAINDICATIONS

4.1 Anaphylaxis to Ceftriaxone or the Cephalosporin Class of Antibacterials, Penicillins or Other Beta-Lactam Antibacterials

Ceftriaxone for Injection, USP is contraindicated in patients who have a history of anaphylaxis to ceftriaxone or the cephalosporin class of antibacterials, penicillins, or other beta-lactam antibacterials [see Warnings and Precautions (5.1)].

5 WARNINGS AND PRECAUTIONS

5.1 Hypersensitivity Reactions to Ceftriaxone, Cephalosporins, Penicillins or Other Drugs

Serious, occasionally fatal, hypersensitivity (anaphylactic) reactions have been reported with ceftriaxone. Before therapy with Ceftriaxone for Injection, USP is instituted, careful inquiry should be made to determine whether the patient has had previous immediate hypersensitivity reactions to ceftriaxone, cephalosporins, penicillins, or other drugs. Exercise caution if this product is to be given to penicillin-sensitive patients because cross-hypersensitivity among beta-lactam antibacterials has been clearly documented and may occur in up to 10% of patients with a history of penicillin allergy. If an allergic reaction to Ceftriaxone for Injection, USP occurs, discontinue the drug. Serious acute hypersensitivity reactions may require treatment with epinephrine and other emergency measures including oxygen, corticosteroids, intravenous fluids, intravenous antihistamines, pressor amines, and airway management, as clinically indicated.

5.2 Interaction with Calcium-Containing Products

Precipitation of ceftriaxone-calcium can occur when Ceftriaxone for Injection, USP is mixed with calcium-containing solutions in the same intravenous administration line. Ceftriaxone for Injection must not be administered simultaneously with calcium-containing intravenous solutions, including continuous calcium-containing infusions, such as parenteral nutrition via a Y-site. However, in patients other than neonates, Ceftriaxone for Injection, USP and calcium-containing solutions may be administered sequentially of one another if the infusion lines are thoroughly flushed between infusions with 0.9% Sodium Chloride Injection or D5W. In vitro studies using adult and neonatal plasma from umbilical cord blood demonstrated that neonates have an increased risk of precipitation of ceftriaxone-calcium. [see Drug Interactions (7.2)]

5.3 Neurological Adverse Reactions

Serious neurological adverse reactions have been reported during postmarketing surveillance with ceftriaxone use. These reactions include encephalopathy (disturbances of consciousness including somnolence, lethargy, and confusion), seizures, myoclonus, and non-convulsive status epilepticus [see Adverse Reactions (6.2)]. Some cases occurred in patients with severe renal impairment who did not receive appropriate dosage adjustment. However, in other cases, neurological adverse reactions occurred in patients receiving an appropriate dosage adjustment. The neurological adverse reactions were reversible and resolved after discontinuation. If neurological adverse reactions associate with Ceftriaxone for Injection therapy occur, discontinue Ceftriaxone for Injection and institute appropriate supportive measures. Make appropriate dosage adjustments in patients with severe renal impairment. [see Dosage and Administration (2.1)].

5.4 Clostridium difficile-associated Diahrrhea

Clostridium difficile-associated diarrhea (CDAD) has been reported with use of nearly all antibacterial agents, including ceftriaxone, and may range in severity from mild diarrhea to fatal colitis. Treatment with antibacterial agents alters the normal flora of the colon leading to overgrowth of C. difficile.

C. difficile produces toxins A and B, which contribute to the development of CDAD. Hypertoxin-producing strains of C. difficile cause increased morbidity and mortality, as these infections can be refractory to antimicrobial therapy and may require colectomy. CDAD must be considered in all patients who present with diarrhea following antibacterial use. Careful medical history is necessary, since CDAD has been reported to occur over two months after the administration of antibacterial agents.

If CDAD is suspected or confirmed, ongoing antibacterial use not directed against C. difficile may need to be discontinued. Appropriate fluid and electrolyte management, protein supplementation, antibacterial treatment of C. difficile, and surgical evaluation should be instituted as clinically indicated.

5.5 Hemolytic Anemia

An immune mediated hemolytic anemia has been observed in patients receiving cephalosporin class antibacterials including ceftriaxone. Severe cases of hemolytic anemia, including fatalities, have been reported during treatment in both adults and children. If a patient develops anemia while on Ceftriaxone for Injection, USP, the diagnosis of a cephalosporin-associated anemia should be considered and Ceftriaxone for Injection, USP stopped until the etiology is determined.

5.6 Gallbladder Sonogram Abnormalities

There have been reports of sonographic abnormalities in the gallbladder of patients treated with ceftriaxone sodium; some of these patients also had symptoms of gallbladder disease. These abnormalities appear on sonography as an echo without acoustical shadowing suggesting sludge or as an echo with acoustical shadowing, which may be misinterpreted as gallstones. The chemical nature of the sonographically detected material has been determined to be predominantly a ceftriaxone-calcium salt. The condition appears to be transient and reversible upon discontinuation of ceftriaxone sodium and institution of conservative management. Therefore, ceftriaxone should be discontinued in patients who develop signs and symptoms suggestive of gallbladder disease and/or the sonographic findings described above.

5.7 Patients with Hepatic and Renal Impairment

Hepatic Impairment: In patients with both hepatic and significant renal disease, Ceftriaxone for Injection dosage should not exceed 2 grams daily.

Renal Impairment: This formulation of Ceftriaxone for Injection USP – Pharmacy Bulk Package bags SmartPak® should not be used in renally impaired patients who require less than the 1 gram dose of ceftriaxone. In patients with both hepatic impairment and significant renal disease, Ceftriaxone for Injection dosage should not exceed 2 grams per day.

5.8 Pancreatitis

Cases of pancreatitis, possibly secondary to biliary obstruction, have been reported in patients treated with ceftriaxone sodium. Most patients presented with risk factors for biliary stasis and biliary sludge (preceding major therapy, severe illness, total parenteral nutrition). A cofactor role of ceftriaxone-related biliary precipitation cannot be ruled out.

5.9 Development of Drug-Resistant Bacteria

Prescribing Ceftriaxone for Injection, USP in the absence of a proven or strongly suspected bacterial infection or a prophylactic indication is unlikely to provide benefit to the patient and increases the risk of the development of drug-resistant bacteria. As with other antibacterial drugs, use of Ceftriaxone for Injection may result in overgrowth of nonsusceptible organisms. Careful observation of the patient is essential. If superinfection occurs during therapy, appropriate measures should be taken.

5.10 Alterations in Prothrombin Time

Alterations in prothrombin times have occurred in patients treated with ceftriaxone sodium. Patients with impaired vitamin K synthesis or low vitamin K stores (e.g., chronic hepatic disease and malnutrition) may require monitoring of prothrombin time during Ceftriaxone for Injection treatment. Vitamin K administration (10 mg weekly) may be necessary if the prothrombin time is prolonged before or during therapy.

6 ADVERSE REACTIONS

The following serious adverse reactions to ceftriaxone are described below and elsewhere in the labeling:

- Hypersensitivity reactions [see Warnings and Precautions (5.1)]
- Ceftriaxone-calcium precipitates [see Warnings and Precautions (5.2) and Drug Interactions (7.2)]
- Clostridium difficile-associated diarrhea [see Warnings and Precautions (5.3)]
- Hemolytic anemia [see Warnings and Precautions (5.4)]

6.1 Clinical Trials Experience

Because clinical trials are conducted under widely varying conditions, adverse reaction rates observed in the clinical trials of a drug cannot be directly compared to rates in the clinical trials of another drug and may not reflect the rates observed in practice. The following reactions occurred in ≤ 6% of the patients:

- Local reactions – pain, induration, tenderness, and phlebitis after intravenous administration.
- Hypersensitivity – rash, pruritus, fever or chills.
- Hematologic – eosinophilia, thrombocytosis, leukopenia, anemia, hemolytic anemia, neutropenia, lymphopenia, thrombocytopenia, and prolongation of the prothrombin time.
- Gastrointestinal – diarrhea, nausea or vomiting, and dysgeusia. The onset of pseudomembranous colitis symptoms may occur during or after antibacterial treatment [see Warnings and Precautions (5.4)].
- Hepatic – elevations of SGOT, SGPT, alkaline phosphatase, bilirubin.
- Renal – elevations of the BUN, creatinine, and the presence of casts in the urine.
- Central Nervous System – headache or dizziness.
- Genitourinary – moniliasis or vaginitis.
- Miscellaneous – diaphoresis and flushing.
- Ceftriaxone-calcium precipitates – Cases of fatal reactions with ceftriaxone-calcium precipitates in lung and kidneys in neonates have been described. In some cases the infusion lines and times of administration of ceftriaxone and calcium-containing solutions differed [see Warnings and Precautions (5.2) and Drug Interactions (7.2)].
- Other observed adverse reactions - abdominal pain, agranulocytosis, allergic pneumonitis, anaphylaxis, basophilia, biliary lithiasis, bronchospasm, colitis, dyspepsia, epistaxis, flatulence, gallbladder sludge, glycosuria, hematuria, jaundice, leukocytosis, lymphocytosis, monocytosis, nephrolithiasis, palpitations, a decrease in the prothrombin time, renal precipitations, seizures, and serum sickness.

6.2 Postmarketing Experience

The following adverse reactions have been reported during postapproval use of ceftriaxone. Because these reactions are reported voluntarily from a population of uncertain size, it is not always possible to readily estimate their frequency or establish a causal relationship to drug exposure.

- Neurologic-Encephalopathy, seizures, myoclonus, and non-convulsive status epilepti us [see Warnings and Precautions (5.3)]

- Gastrointestinal – stomatitis and glossitis
- Genitourinary – oliguria
- Dermatologic – exanthema, allergic dermatitis, urticaria, edema

Cases of severe cutaneous adverse reactions (erythema multiforme, Stevens-Johnson syndrome or Lyell’s syndrome/toxic epidermal necrolysis) have been reported.

Anaphylaxis (including anaphylactic shock, transient leukopenia, neutropenia, agranulocytosis and thrombocytopenia) has been reported.

6.3 Cephalosporin-class Adverse Reactions

In addition to the adverse reactions listed above that have been observed in patients treated with ceftriaxone, the following adverse reactions and altered laboratory tests have been reported for cephalosporin-class antibacterials:

- Adverse Reactions: Allergic reactions, drug fever, serum sickness-like reaction, renal dysfunction, toxic nephropathy, reversible hyperactivity, hypertonia, hepatic dysfunction including cholestasis, aplastic anemia, hemorrhage, and superinfection.
- Altered Laboratory Tests: Positive direct Coombs’ test, false-positive test for urinary glucose, and elevated LDH.

7 DRUG INTERACTIONS

7.1 Vancomycin, Amsacrine, Aminoglycosides, and Fluconazole

Vancomycin, amsacrine, aminoglycosides, and fluconazole are physically incompatible with ceftriaxone in admixtures [see Dosage and Administration (2.3)].

7.2 Calcium-containing Products

Precipitation of ceftriaxone-calcium can occur when Ceftriaxone for Injection is mixed with calcium-containing solutions in the same intravenous administration line. Ceftriaxone for Injection, USP must not be administered simultaneously with calcium-containing intravenous solutions. Ceftriaxone for Injection and calcium-containing solutions can be administered sequentially [see Warnings and Precautions (5.2)]

8 USE IN SPECIFIC POPULATIONS

8.1 Pregnancy

Pregnancy Category B.

Reproductive studies have been performed in mice, rats, and primates at intravenous doses of 625, 586, and 84 mg/kg/day, respectively without evidence of embryotoxicity, fetotoxicity, or teratogenicity. These doses are approximately 1.5, 2.8, and 0.8 times the recommended clinical dose of 2 grams/day based on body surface area comparisons.

There are, however, no adequate and well-controlled studies in pregnant women. Because animal reproductive studies are not always predictive of human response, this drug should be used during pregnancy only if clearly needed.

Ceftriaxone was tested in a Segment III (pre-postnatal) study in rats at intravenous doses of up to 586 mg/kg/day approximately 2.8 times (mg/m^2 comparison) the recommended daily dose of 2 grams/day. No adverse effects were noted on various reproductive parameters during gestation and lactation, including postnatal growth, functional behavior, and reproductive ability of the offspring.

8.3 Nursing Mothers

Ceftriaxone is excreted in human breast milk. Caution should be exercised when Ceftriaxone for Injection is administered to a nursing woman.

8.4 Pediatric Use

Ceftriaxone for Injection USP, Pharmacy Bulk Package bag, SmartPak® should not be used in pediatric patients who require less than the 1 gram dose of ceftriaxone. To prevent unintentional overdose, this product should not be used in pediatric patients who require less than the adult 1 gram dose of ceftriaxone.

8.5 Geriatric Use

Of the total number of subjects in clinical studies of ceftriaxone sodium, 32% were 60 and over. No overall differences in safety or effectiveness were observed between these subjects and younger subjects, and other reported clinical experience has not identified differences in responses between the elderly and younger patients, but greater sensitivity of some older individuals cannot be ruled out.

Ceftriaxone is known to be substantially excreted by the kidney, and the risk of adverse reactions to this drug may be greater in patients with impaired renal function. Because elderly patients are more likely to have decreased renal function, care should be taken in dose selection, and it may be useful to monitor renal function.

The pharmacokinetics of ceftriaxone were only minimally altered in geriatric patients compared to healthy adult subjects, and dosage adjustments are not necessary for geriatric patients with ceftriaxone dosages up to 2 grams per day [see Clinical Pharmacology (12)].

10 OVERDOSAGE

Ceftriaxone overdosage has been reported in patients with severe renal impairment. Reactions have included neurological outcomes, including encephalopathy, seizures, myoclonus, and non -convulsive status epilepticus. In the event of overdosage discontinue Ceftriaxone for Injection therapy and provide general supportive treatment [see Dosage and Administration (2.1) and Warnings and Precautions (5.3)].

In the case of overdosage, drug concentration would not be reduced by hemodialysis or peritoneal dialysis. There is no specific antidote. Treatment of overdosage should be symptomatic.

11 DESCRIPTION

Ceftriaxone for Injection, USP, Pharmacy Bulk Package bag SmartPak® should be used only in patients who require a 1 gram dose and not any fraction thereof.

Ceftriaxone for Injection USP, Pharmacy Bulk Package bag SmartPak® should not be used in patients who require less than the 1 gram dose of ceftriaxone.

Ceftriaxone for Injection, USP, is a sterile, semisynthetic, broad-spectrum cephalosporin antibacterial for intravenous administration. Ceftriaxone sodium is (6R,7R)-7-[2-(2-Amino-4-thiazolyl)glyoxylamido]-8-oxo-3-[[(1,2,5,6-tetrahydro-2-methyl-5,6-dioxo-as-triazin-3-yl)thio]methyl]-5-thia-1-azabicyclo[4.2.0]oct-2-ene-2-carboxylic acid, 7^2-(Z)-(O-methyloxime), disodium salt, sesquaterhydrate.

The chemical formula of ceftriaxone sodium is C18H16N8Na2O7S3•3.5H2O. It has a calculated molecular weight of 661.60 and the following structural formula:

Ceftriaxone sodium is a white to yellowish-orange crystalline powder, which is readily soluble in water, sparingly soluble in methanol and very slightly soluble in ethanol. The pH of a 1% aqueous solution is approximately 6.7. The color of ceftriaxone sodium solutions ranges from light yellow to amber, depending on the length of storage and concentration. Each Pharmacy Bulk Package contains approximately 83 mg (3.6 mEq) of sodium per 1 gram of ceftriaxone activity. Ceftriaxone for Injection, USP is supplied in 100 grams SmartPak® Pharmacy Bulk Packages bags equivalent. Each SmartPak® Pharmacy Bulk Package bag contains ceftriaxone sodium, USP equivalent to 100 grams of ceftriaxone.

BEFORE ADMINISTRATION, THIS PHARMACY BULK PACKAGE REQUIRES RECONSTITUTION USING STERILE WATER FOR INJECTION, USP TO A CONCENTRATION OF 100 mg per mL AND FURTHER DILUTION IN 50 mL OF A COMPATIBLE SOLUTION AND INFUSED INTRAVENOUSLY OVER 30 MINUTES.

THIS PRODUCT IS NOT INTENDED TO BE USED IN PEDIATRIC PATIENTS AND RENALLY IMPAIRED PATIENTS WHO REQUIRE LESS THAN A 1 GRAM DOSE.

A Pharmacy Bulk Package is a container of a sterile preparation for parenteral use that contains many single doses. The contents are intended for use in a pharmacy admixture service and are restricted to the preparation of admixtures for intravenous infusion.

12 CLINICAL PHARMACOLOGY

12.1 Mechanism of Action

Ceftriaxone is an antibacterial drug. [see Microbiology (12.4)]

12.3 Pharmacokinetics

Average plasma concentrations of ceftriaxone following a single 30-minute intravenous (I.V.) infusion of a 0.5, 1 or 2 g dose in healthy subjects are presented in Table 3. Multiple intravenous doses ranging from 0.5 to 2 g at 12- to 24-hour intervals resulted in 15% to 36% accumulation of ceftriaxone above single dose values.

TABLE 3: Ceftriaxone Plasma Concentrations After Single Dose Administration

Dose/Route | Average Plasma Concentrations (mcg/mL)
0.5 hr |  | 1 hr | 2 hr | 4 hr | 6 hr | 8 hr | 12 hr | 16 hr | 24 hr
0.5 gram I.V. [I.V. doses were infused at a constant rate over 30 minutes.] | 82 | 59 | 48 | 37 | 29 | 23 | 15 | 10 | 5
1 gram I.V. | 151 | 111 | 88 | 67 | 53 | 43 | 28 | 18 | 9
2 grams I.V. | 257 | 192 | 154 | 117 | 89 | 74 | 46 | 31 | 15

Over a 0.15 to 3 g dose range in healthy adult subjects, the mean elimination half-life ranged from 5.8 to 8.7 hours, plasma clearance ranged from 0.58 to 1.45 L/hour, and renal clearance ranged from 0.32 to 0.73 L/hour.

Distribution

Ceftriaxone is reversibly bound to human plasma proteins and the binding of ceftriaxone decreases with increasing concentration from a value of 95% at plasma concentrations less than 25 mcg/mL to 85% at plasma concentration of 300 mcg/mL. Over a 0.15 to 3 g dose range in healthy adult subjects, the apparent volume of distribution ranged from 5.8 to 13.5 L.

Ceftriaxone crosses the blood placenta barrier.

Ceftriaxone penetrates the inflamed meninges of infants and pediatric patients. The average values of maximum plasma concentration, cerebrospinal fluid (CSF) concentrations, elimination half-life, plasma clearance and volume of distribution after a 50 mg/kg intravenous dose and after a 75 mg/kg intravenous dose in pediatric patients suffering from bacterial meningitis are shown in Table 4.

TABLE 4: Average Pharmacokinetic Parameters of Ceftriaxone in Pediatric Patients with Meningitis

 | 50 mg/kg I.V. | 75 mg/kg I.V.
Maximum Plasma Concentrations (mcg/mL) | 216 | 275
Elimination Half-life (hr) | 4.6 | 4.3
Plasma Clearance (mL/hr/kg) | 49 | 60
Volume of Distribution (mL/kg) | 338 | 373
CSF Concentration – inflamed meninges (mcg/mL) | 5.6 | 6.4
Range (mcg/mL) | 1.3-18.5 | 1.3-44
Time after dose (hr) | 3.7 (±1.6) | 3.3 (±1.4)

After a 1 gram intravenous dose, average concentrations of ceftriaxone, determined from 1 to 3 hours after dosing, were 581 mcg/mL in the gallbladder bile, 788 mcg/mL in the common duct bile, 898 mcg/mL in the cystic duct bile, 78.2 mcg/gram in the gallbladder wall compared to a corresponding concentration of 62.1 mcg/mL in plasma.

Excretion

Ceftriaxone concentrations in urine are shown in Table 5.

TABLE 5: Urinary Concentrations of Ceftriaxone After Single Dose Administration

Average Urinary Concentrations (mcg/mL)
Dose/Route | 0-2 hr | 2-4 hr | 4-8 hr | 8-12 hr | 12-24 hr | 24-48 hr
0.5 gram I.V. | 526 | 366 | 142 | 87 | 70 | 15
1 gram I.V. | 995 | 855 | 293 | 147 | 132 | 32
2 grams I.V. | 2692 | 1976 | 757 | 274 | 198 | 40

Thirty-three percent to 67% of a ceftriaxone dose was excreted in the urine as unchanged drug, and the remainder was secreted in the bile and ultimately found in the feces as microbiologically inactive compounds.

The elimination of ceftriaxone is not altered by probenecid.

Special Populations

Average pharmacokinetic parameters of ceftriaxone in healthy subjects, elderly subjects, subjects with renal impairment, and subjects with liver disease are summarized in Table 6. Compared to healthy adult subjects, the pharmacokinetics of ceftriaxone were only minimally altered in elderly subjects and in patients with renal or hepatic impairment; therefore, dosage adjustments are not necessary for these patients with ceftriaxone dosages up to 2 grams per day. Ceftriaxone was not removed to any significant extent from the plasma by hemodialysis. In 6 of 26 dialysis patients, the elimination rate of ceftriaxone was markedly reduced, suggesting that plasma concentrations of ceftriaxone should be monitored in these patients to determine if dosage adjustments are necessary [see Dosage and Administration (2.1) and Warnings and Precautions (5.7)].

TABLE 6: Average Pharmacokinetic Parameters of Ceftriaxone in Humans

Subject Group | Elimination Half-Life (hr) | Plasma Clearance (L/hr) | Volume of Distribution (L)
Healthy Subjects [Dose ranged from 0.15 to 3 grams] | 5.8-8.7 | 0.58-1.45 | 5.8-13.5
Elderly Subjects (mean age, 70.5 yr) | 8.9 | 0.83 | 10.7
Patients with Renal Impairment
Hemodialysis Patients (0-5 mL/min) [Creatinine clearance.] | 14.7 | 0.65 | 13.7
Severe (5-15 mL/min) | 15.7 | 0.56 | 12.5
Moderate (16-30 mL/min) | 11.4 | 0.72 | 11.8
Mild (31-60 mL/min) | 12.4 | 0.70 | 13.3
Patients with Liver Disease | 8.8 | 1.1 | 13.6

Drug Interactions

Interaction with Calcium: Two in vitro studies, one using adult plasma and the other neonatal plasma from umbilical cord blood, have been carried out to assess interaction of ceftriaxone and calcium. Ceftriaxone concentrations up to 1 mM (in excess of concentrations achieved in vivo following administration of 2 grams ceftriaxone infused over 30 minutes) were used in combination with calcium concentrations up to 12 mM (48 mg/dL). Recovery of ceftriaxone from plasma was reduced with calcium concentrations of 6 mM (24 mg/dL) or higher in adult plasma or 4 mM (16 mg/dL) or higher in neonatal plasma. This may be reflective of ceftriaxone-calcium precipitation.

12.4 Microbiology

Mechanism of Action

Ceftriaxone is a bactericidal agent that acts by inhibition of bacterial cell wall synthesis. Ceftriaxone has activity in the presence of some beta-lactamases, both penicillinases and cephalosporinases, of Gram-negative and Gram-positive bacteria.

Mechanism of Resistance

Resistance to ceftriaxone is primarily through hydrolysis by beta-lactamase, alteration of penicillin-binding proteins (PBPs), and decreased permeability.

Interaction with Other Antimicrobials

In an in vitro study antagonistic effects have been observed with the combination of chloramphenicol and ceftriaxone.

Antibacterial Activity

Ceftriaxone has been shown to be active against most isolates of the following bacteria, both in vitro and in clinical infections described in the INDICATIONS AND USAGE (1) section.

- Gram-negative Bacteria
  - Acinetobacter calcoaceticus
  - Enterobacter aerogenes
  - Enterobacter cloacae
  - Escherichia coli
  - Haemophilus influenzae
  - Haemophilus parainfluenzae
  - Klebsiella oxytoca
  - Klebsiella pneumoniae
  - Moraxella catarrhalis
  - Morganella morganii
  - Neisseria gonorrhoeae
  - Neisseria meningitidis
  - Proteus mirabilis
  - Proteus vulgaris
  - Pseudomonas aeruginosa
  - Serratia marcescens
- Gram-positive Bacteria
  - Staphylococcus aureus
  - Staphylococcus epidermidis
  - Streptococcus pneumoniae
  - Streptococcus pyogenes
  - Viridans group streptococci
- Anaerobic Bacteria
  - Bacteroides fragilis
  - Clostridium species
  - Peptostreptococcus species

The following in vitro data are available, but their clinical significance is unknown. At least 90 percent of the following microorganisms exhibit an in vitro minimum inhibitory concentration (MIC) less than or equal to the susceptible breakpoint for ceftriaxone. However, the efficacy of ceftriaxone in treating clinical infections due to these microorganisms has not been established in adequate and well-controlled clinical trials.

- Gram-negative Bacteria
  - Citrobacter diversus
  - Citrobacter freundii
  - Providencia species (including Providencia rettgeri)
  - Salmonella species (including Salmonella typhi)
  - Shigella species
- Gram-positive Bacteria
  - Streptococcus agalactiae
- Anaerobic Bacteria
  - Porphyromonas (Bacteroides) melaninogenicus
  - Prevotella (Bacteroides) bivius

Susceptibility Testing

For specific information regarding susceptibility test interpretive criteria and associated test methods and quality control standards recognized by FDA for this drug, please see: https://www.fda.gov/STIC

13 NONCLINICAL TOXICOLOGY

13.1 Carcinogenesis, Mutagenesis, Impairment of Fertility

Carcinogenesis

Considering the maximum duration of treatment and the class of the compound, carcinogenicity studies with ceftriaxone in animals have not been performed. The maximum duration of animal toxicity studies was 6 months.

Mutagenesis

Genetic toxicology tests included the Ames test, a micronucleus test and a test for chromosomal aberrations in human lymphocytes cultured in vitro with ceftriaxone. Ceftriaxone showed no potential for genotoxic activity in these studies.

Impairment of Fertility

Ceftriaxone produced no impairment of fertility when given intravenously to rats at daily doses up to 586 mg/kg/day, approximately 2.8 times (mg/m^2 comparison) the recommended clinical dose of 2 grams/day.

13.2 Animal Toxicology and/or Animal Pharmacology

Concretions consisting of the precipitated calcium salt of ceftriaxone have been found in the gallbladder bile of dogs and baboons treated with ceftriaxone. These appeared as a gritty sediment in dogs that received 100 mg/kg/day for 4 weeks.

A similar phenomenon has been observed in baboons but only after a protracted dosing period (6 months) at higher dose levels (335 mg/kg/day or more).

16 HOW SUPPLIED/STORAGE AND HANDLING

Ceftriaxone for Injection, USP is available in the following SmartPak® Pharmacy Bulk Package bags:

100 grams* One Pharmacy Bulk Package bag Product No. 6100 NDC 66288-6100-1.

*Each 100 gram Pharmacy Bulk Package bag contains sterile ceftriaxone sodium equivalent to 100 grams of ceftriaxone

SmartPak® system components are not made with natural rubber latex.

Precautions

As with other cephalosporins, reconstituted Ceftriaxone for Injection tends to darken depending on storage conditions within the stated recommendations. However, product potency is not adversely affected.

Use only if prepared solution is clear and free from particulate matter.

Storage Conditions

Prior to reconstitution, store Ceftriaxone for Injection sterile powder at room temperature 20º-25ºC (68º-77ºF) [see USP Controlled Room Temperature] and protected from light.

17 PATIENT COUNSELING INFORMATION

- Advise patients that neurological adverse reactions could occur with Ceftriaxone for Injection use. Instruct patients or their caregivers to inform their healthcare provider at once of any neurological signs and symptoms, including encephalopathy (disturbance of consciousness including somnolence, lethargy, and confusion), seizures, myoclonus, and non-convulsive status epilepticus, for immediate treatment, or discontinuation of Ceftriaxone for Injection [see Warnings and Precautions (5.3)].
- Patients should be advised that allergic reactions, including serious allergic reactions could occur and that serious reactions require immediate treatment and discontinuation of ceftriaxone. Patients should report to their health care provider any previous allergic reactions to ceftriaxone, cephalosporins, penicillins, or other similar antibacterials.
- Advise patients of neurological adverse reactions that could occur with Ceftriaxone for Injection, USP use. Instruct patients to inform a healthcare provider at once of any neurological signs and symptoms, including encephalopathy (disturbance of consciousness including confusion, hallucinations, stupor, and coma), myoclonus, and seizures, for immediate treatment, dosage adjustment, or discontinuation of Ceftriaxone for Injection, USP.
- Patients should be advised that diarrhea is a common problem caused by antibacterials, which usually ends when the antibacterial is discontinued. Sometimes after starting treatment with antibacterials, patients can develop watery and bloody stools (with or without stomach cramps and fever) even as late as two or more months after having taken the last dose of the antibacterial. If this occurs, patients should contact a physician as soon as possible.
- Patients should be counseled that antibacterial drugs including ceftriaxone, should only be used to treat bacterial infections. They do not treat viral infections (e.g., the common cold). When Ceftriaxone for Injection, USP is prescribed to treat a bacterial infection, patients should be told that although it is common to feel better early in the course of therapy, the medication should be taken exactly as directed. Skipping doses or not completing the full course of therapy may (1) decrease the effectiveness of the immediate treatment and (2) increase the likelihood that bacteria will develop resistance and will not be treatable by ceftriaxone or other antibacterial drugs in the future.

Rx only
SmartPak is a registered trademark of Samson Medical Technologies, L.L.C.
C6100d
SAMSON
MEDICAL TECHNOLOGIES L.L.C.
Cherry Hill, NJ 08003, USA
by
ACS Dobfar S.p.A.
20067 Tribiano (Milano) Italy
Manufactured for

PRINCIPAL DISPLAY PANEL - Pharmacy Bulk Package - Ceftriaxone bag label

NDC 66288-6100-1 SMARxTPAK

CEFTRIAXONE FOR INJECTION, USP

PHARMACY BULK PACKAGE -
NOT FOR DIRECT INFUSION

100 grams [ONE HUNDRED GRAMS] per Pharmacy Bulk Package Bag

FOR INTRAVENOUS USE ONLY

NOT TO BE DISPENSED AS A UNIT

Rx Only

Sterile, Nonpyrogenic, Preservative-Free

Each 100 gram Pharmacy Bulk Package contains sterile ceftriaxone sodium equivalent to 100 grams of ceftriaxone. The sodium content is 83 mg (3.6 mEq) per gram of ceftriaxone activity.

Use this formulation only in patients who require a 1 gram dose. Contains 100 doses (1 gram per dose). See package insert. USUAL DOSAGE: See package insert.

Prior to reconstitution, store dry powder at 20° to 25°C (68° to 77°F). [See USP Controlled Room Temperature] Protect from light. After reconstitution, dilute and use promptly. DISCARD BAG WITHIN 4 HOURS AFTER INITIAL ENTRY. See package insert for full information.

THIS PHARMACY BULK PACKAGE IS INTENDED FOR PREPARING MANY SINGLE DOSES IN A PHARMACY ADMIXTURE PROGRAM.

Approximate Concentration | Amount of Sterile Water for Injection
1 gram/10 mL | 950 mL

See package insert for detailed reconstitution, final dilution, and administration instructions.

PROTECT FROM LIGHT. THE INNER BAG SHOULD BE RETAINED IN THE OUTER BAG UNTIL TIME OF USE.

SmartPak® system components are not made with natural rubber latex.

Manufactured for
SAMSON
MEDICAL TECHNOLOGIES L.L.C.
Cherry Hill, NJ 08003,

Date entered

Time of entry

Discard within 4 hours